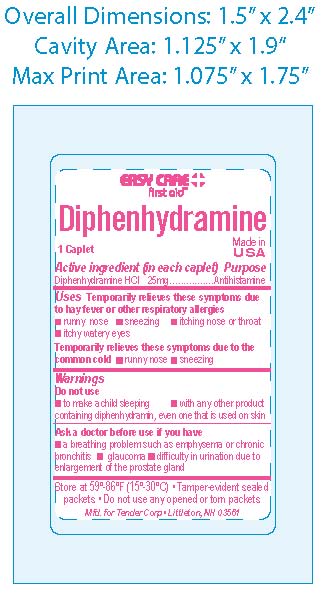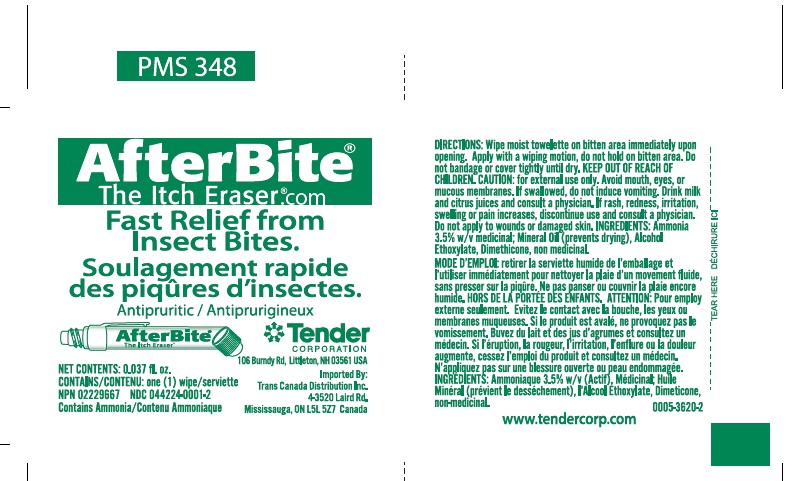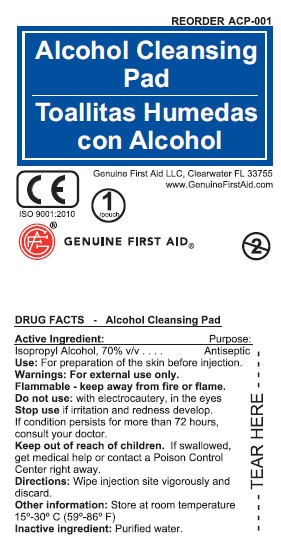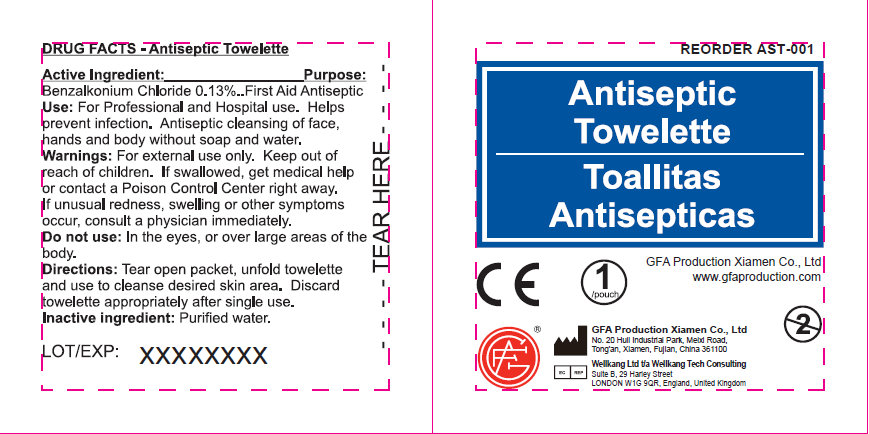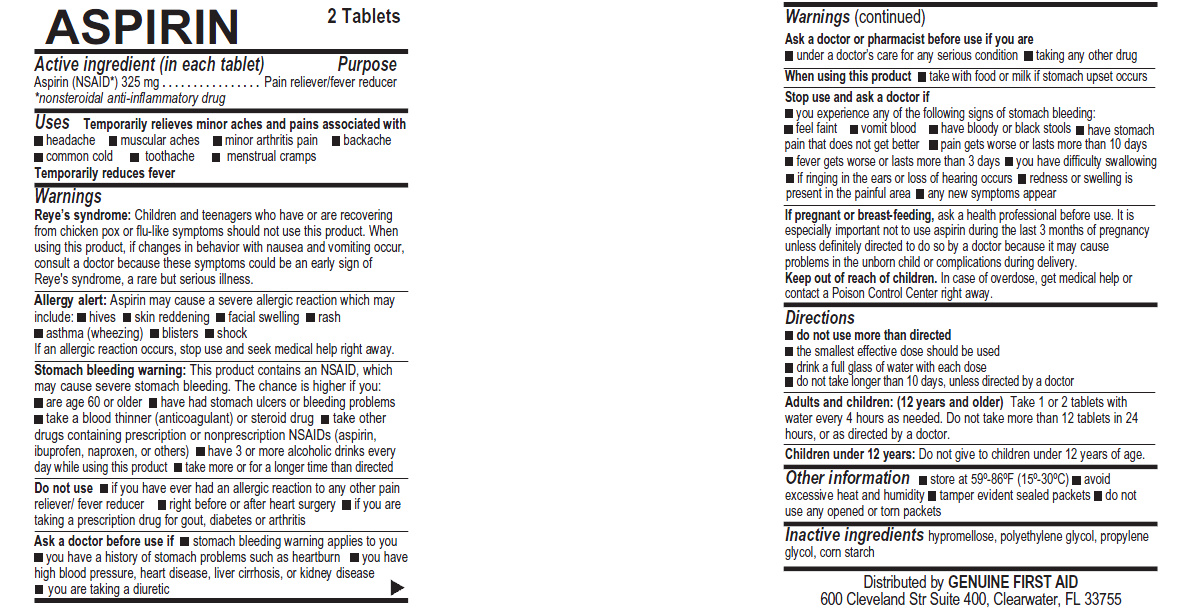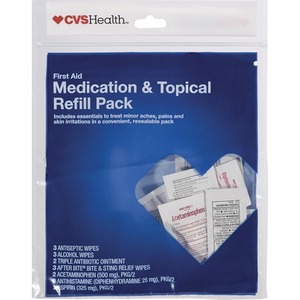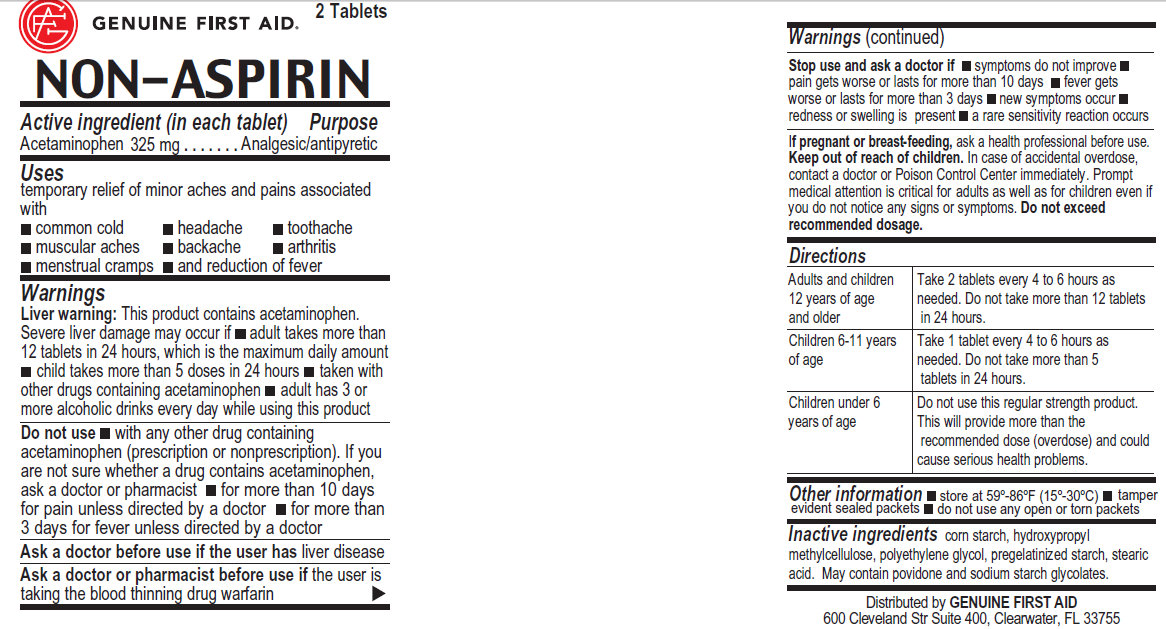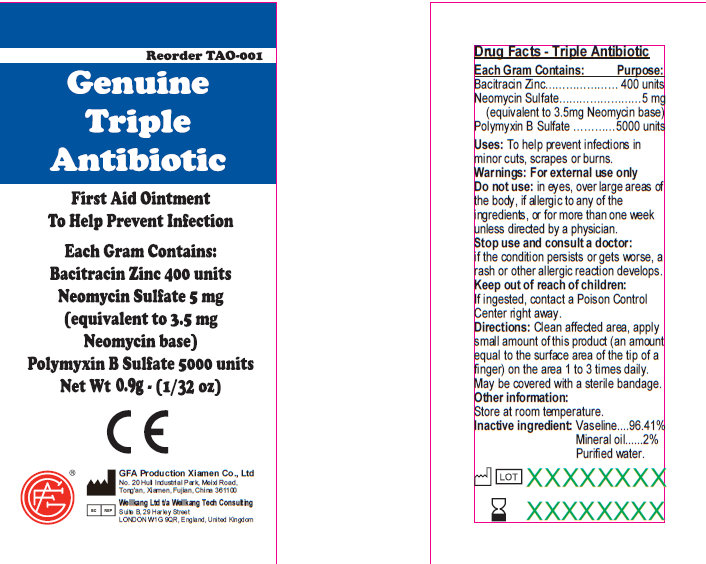 DRUG LABEL: CVS Health Medication and Topical Refill Pouch
NDC: 69842-404 | Form: KIT | Route: ORAL
Manufacturer: CVS
Category: otc | Type: HUMAN OTC DRUG LABEL
Date: 20170118

ACTIVE INGREDIENTS: DIPHENHYDRAMINE HYDROCHLORIDE 25 mg/1 1; ISOPROPYL ALCOHOL 700 mg/1 mL; AMMONIA 30 mg/1 mL; ACETAMINOPHEN 500 mg/1 1; BENZALKONIUM CHLORIDE 1.3 mg/1 mL; BACITRACIN ZINC 400 [iU]/1 g; NEOMYCIN SULFATE 5 mg/1 g; POLYMYXIN B SULFATE 5000 [iU]/1 g; ASPIRIN 325 mg/1 1
INACTIVE INGREDIENTS: GELATIN; FD&C BLUE NO. 1; STARCH, CORN; D&C RED NO. 28; FD&C RED NO. 40; WATER; DIMETHICONE 1000; LIGHT MINERAL OIL; C12-13 ALCOHOLS; WATER; POLYETHYLENE GLYCOL, UNSPECIFIED; STARCH, CORN; POVIDONE; STEARIC ACID; WATER; PETROLATUM; WATER; MINERAL OIL; HYPROMELLOSES; PROPYLENE GLYCOL; POLYETHYLENE GLYCOLS; STARCH, CORN

CVS Health Medication & Topical Refill Pouch

Active Ingredients - Genuine Triple Antibiotic

Active Ingredient: .........Bacitracin Zinc 400 units

Neomycin Sulfate 5mg (equivalent to 3.5 mg Neomycin base)

Polymyxin B Sulfate 5000 units

Purpose - Genuine Triple Antibiotic

Triple Antibiotic

Uses - Genuine Triple Antibiotic

To help prevent infection in:
minor cuts; scrapes; burns

Warnings - Genuine Triple Antibiotic

For external use only

DO NOT USE - Genuine Triple Antibiotic

Do not use: in eyes; over large areas of the body;

If allergic to any of the ingredients; for more than one week unless directed by a physician.

Stop Use - Genuine Triple Antibiotic

Stop use and consult a doctor:

if the condition persists or gets worse; a rash or other allergic reaction develops

Keep Out of Reach of Children - Genuine Triple Antibiotic

Keep out of reach of children.

If ingested, contact a Poison

Control Center right away.

Directions - Genuine Triple Antibiotic

Directions: clean affected area; apply small amount of this product (an amount equal to the surface area of the tip of a finger) on the area 1 to 3 times daily; may be covered with a sterile bandage

Storage and Handling - Genuine Triple Antibiotic

Other information:

Store at room temperature.

Inactive Ingredients - Genuine Triple Antibiotic

Vaseline
Mineral Oil
Purified Water

Active Ingredients - Antiseptic

Active Ingredient:

Benzalkonium Chloride 0.13

Purpose - Antiseptic

Antiseptic

Use - Antiseptic

For Professional and Hospital use. Helps prevent infection. Antiseptic cleansing of face, hands and body without soap and water.

Warnings - Antiseptic

Warning: For external use only.

Keep out of reach of children - Antiseptic

Keep out of reach of children: If swallowed, get medical help or contact a Poison Control Center right away.

Stop Use - Antiseptic

Stop use if unusual redness, swelling or other symptoms occur. Consult a physician immediately.

Do Not Use - Antiseptic

Do not use in the eyes or over large areas of the body.

Directions - Antiseptic

Tear open packet, unfold towelette and use to cleanse desired skin area. Discard towelette appropriately after single use.

Inactive Ingredients - Antiseptic

Inactive Ingredient: Purified water

Active Ingredients - Non-Aspirin

Acetaminophen 500 mg

Purpose - Non Aspirin

Analgesic/antipyretic

Uses - Non Aspirin

temporary relief of minor aches and pains associated with:

common cold; headache; toothache; muscular aches; backache; arthritis; menstrual cramps; and reduction of fever

Warnings - Non Aspirin

Liver warning: This product contains acetaminophen.

Severe liver damage may occur if: adult takes more than 12 tablets in 24 hours, which is the maximum daily amount; child takes more than 5 doses in 24 hours; taken with other drugs containing acetaminophen; adult has 3 or more alcoholic drinks every day while using this product

Do Not Use - Non Aspirin

with any other drug containing acetaminophen (prescription or nonprescription). If you are not sure whether a drug contains acetaminophen, ask a doctor or pharmacist; for more than 10 days for pain unless directed by a doctor; for more than 3 days for fever unless directed by a doctor

Ask a Doctor - Non Aspirin

Ask a doctor before use if the user has liver disease

Ask a doctor or pharmacist before use if the user is taking the blood thinning drug warfarin

Stop Use - Non Aspirin

Stop use and ask a doctor if: symptoms do not improve; pain gets worse or lasts for more than 10 days; fever gets worse or lasts for more than 3 days; new symptoms occur; redness or swelling is present; a rare sensitivity reaction occurs

Pregnancy - Non Aspirin

If pregnant or breast-feeding, ask a health professional before use.

Keep Out of Reach of Children - Non Aspirin

Keep out of reach of children. In case of accidental overdose, contact a doctor or Poison Control Center immediately. Prompt
medical attention is critical for adults as well as for children even if
you do not notice any signs or symptoms. Do not exceed recommended dosage

Inactive Ingredients - Non Aspirin

Cornstarch, polyethylene glycol, stearic acid, povidone

Directions - Non Aspirin

Directions

Adults and Children Take 2 tablets every 4 to 6 hours as

12 years of age needed. Do not take more than 12 tablets

or older in 24 hours.

Children 6-11 years Take 1 tablet every 4 to 6 hours as

of age needed. Do not take more than 5

tablets in 24 hours.

Children under 6 Do not use this regular strength product.

years of age This will provide more than the

recommended dose (overdose) and could

cause serious health problems.

Storage and Handling - Non Aspirin

Store at 59-86 degree F (15-30 degree C)

tamper evident sealed packets; do not use any open or torn packets

Active Ingredients - After Bite

Active Ingredient:

Ammonia 3.5%

Purpose - After Bite

Counterirritant

Uses - After Bite

Temporarily protects and helps relieve minor skin irriatation and itching due to

- insect bites and stings
- poison ivy, oak or sumac

Warnings - After Bite

Warning: For external use only.

Keep Out of Reach of Children - After Bite

Keep out of reach of children: If swallowed, get medical help or contact a Poison Control Center right away.

Stop Use - After Bite

Stop use and ask a doctor if

- condition worsens
- symptoms last more than 7 days or clear up and occur again within a few days

When Using - After Bite

Do not get into eyes

DIrections - After Bite

Adults and children under 2 years and older dab directly on bite or sting, rub gently and re-apply as needed

Children under 2 years ask a doctor

Active Ingredient - Aspirin

Aspirin (NSAID*) 325mg

*nonsteroidal anti-inflammatory drug

Purpose

Pain Releiver / Fever Reducer

Uses - Aspirin

Temporarily relieves minor aches and pains associated with: headache; muscular aches; minor arthritis pain; backache; common cold; toothache; mentrual cramps; temporarily reduces fever

Warnings

Reye's syndrome: Children and teenagers who have or are recovering from chicken pox of flu-like symptoms should not use this product. When using this product, if changes in behavior with nausea and vomiting occur, consult a doctor because these symptoms could be an early sign of Reye's syndrome, a rare but serious illness.

Allergy Alert: Aspirin may cause a severe allergic reaction which may include: hives, skin reddening, facial swelling, rash, asthma (wheezing), blisters, shock. If an allergic reaction occurs, stop use and seek medical help right away.

Stomach bleeding warning: This contains an NSAID, which may cause severe stomach bleeding. The change is higher if you: are age 60 or older; have had stomach ulcers or bleeding problems; take a blood thinner (anticoagulant) or steroid drug; take other drugs containing prescription or nonprescription NSAIDs (aspirin, ibuprofen, naproxen, or others), have 3 or more alcoholic drinks everyday while using this product, take more for a longer time than directed

Do Not Use - Aspirin

Do not use if you have ever had an allergic reaction to any other pain reliever/fever reducer; right before or after heart surgery; if you are taking a prescription drug for gout, diabetes or arthritis.

Ask a doctor before use if: stomach bleeding warning applies to you; you have a history of stomach problems such as heartburn; you have high blood pressure, heart disease, liver cirrhosis or kidney disease; you are taking a diuretic.

Ask a doctor or pharmacist before use if you are: under a doctor's care for any serious condition; taking any other drug.

When using this product: Take with food or milk if stomach upset occurs.

Stop Use and ask a Doctor - Aspirin

Stop Use and ask a Doctor if:

You experience any of the following signs of stomach bleeding, you feel faint, vomit blood, have bloody or black stools, have stomach pain that does not get better, pain gets worse or lasts more than 10 days, fever gets worse or lasts more than 3 days, you have difficulty swallowing, if ringing in the ears or loss of hearing occurs, redness or swelling is present in painful areas, or any new symptoms appear.

If pregnant or breast-feeding, ask a health professional before use. It is especially important not to use aspirin during the last 3 months of pregnancy unless directed to do so by a doctor because it may cause problems in the unborn child or complications during delivery.

Keep out of reach of Children. In case of overdose, get medical help or contact a poison control center right away.

Directions - Aspirin

Do not use more than directed - the smallest effective dose should be used.

Drink a full glass of water with each dose.

Do not take longer than 10 days, unless directed by a doctor.

Adults and Children (12 years and older): take 1 or 2 tablets with water every 4 hours as needed. Do not take more then 12 tablets in 24 hours, or as directed by a doctor.

Children under 12 years: Do not give to children under 12 years of age.

Avoid excessive heat and humidity, do not use any open or torn packets.

Inactive Ingredients - Aspirin

hypromellose, polyethylene glycol, propylene glycol, corn starc

Active Ingredient - Diphenhydramine

Diphenhydramine Hydrochloride 25mg

Purpose - Diphenhydramine

Antihistimine

Use - Diphenhydramine

Temporarily relieves the following symptoms associated with hay fever or oother upper respiratory allergies: runny nose, sneezing, itching of the nose or throat, itchy, watery eyes

Warnings

Ask a doctor before use if you have: a breathing problem such as emphyseme or chronic bronchitis, glaucoma, difficulty in urination due to enlargement of the prostate gland; or if you are: taking any drugs for asthma, sedatives or tranquilizers.

When using this product: Drowziness may occur, avoid alcoholic beverages.

Alcohol, sedatives and tranquilizers may increase the drowziness effect. Use caution when driving a motor vehicle or operating machinery. Excitality may occur, especially in children.

Keep out of Reach of Children

Do not exceed recommended dosage. Keep this and all drugs out of reach of children. In case of accidental overdose, contact a physician or poison control center immediately. As with any drug, if you are pregnant or nursing a baby, seek the advice of a health professional before using the product.

Dosage - Diphenhydramine

Adults and Children (12 Years and older) - take 1 capsule every 4 to 6 hours as needed. Do not take more than 12 tablets in 24 hours, or as directed by a doctor.

Children under 12 years - do not give to children under 12 years unless directed by a doctor

Inactive Ingredients

DandC Red 28, FDandC Blue 1, FDandC Red 40, gelatin, starch

Active Ingredient - Alcohol Pad

Isopropyl Alcohol 70%

Uses - Alcohol Prep Pad

For preparation of the skin before injection

Warnings - Alcohol Prep Pad

For External Use Only

Flammable - Keep away from fire or flame

Do Not Use - with electrocautery, in eyes

Stop Use and Ask a Doctor if - Irritation or redness develop and persists for more than 72 hours

Keep out of Reach of Children

If Swallowed, get medical help or contact a poison control center right away

Directions - Alcohol Prep Pad

Tear Open packet, unfold and use as and wipe injection site vigorously and discard.

Store at Room Temperature

Inactive Ingredients - Alcohol Pad

Water